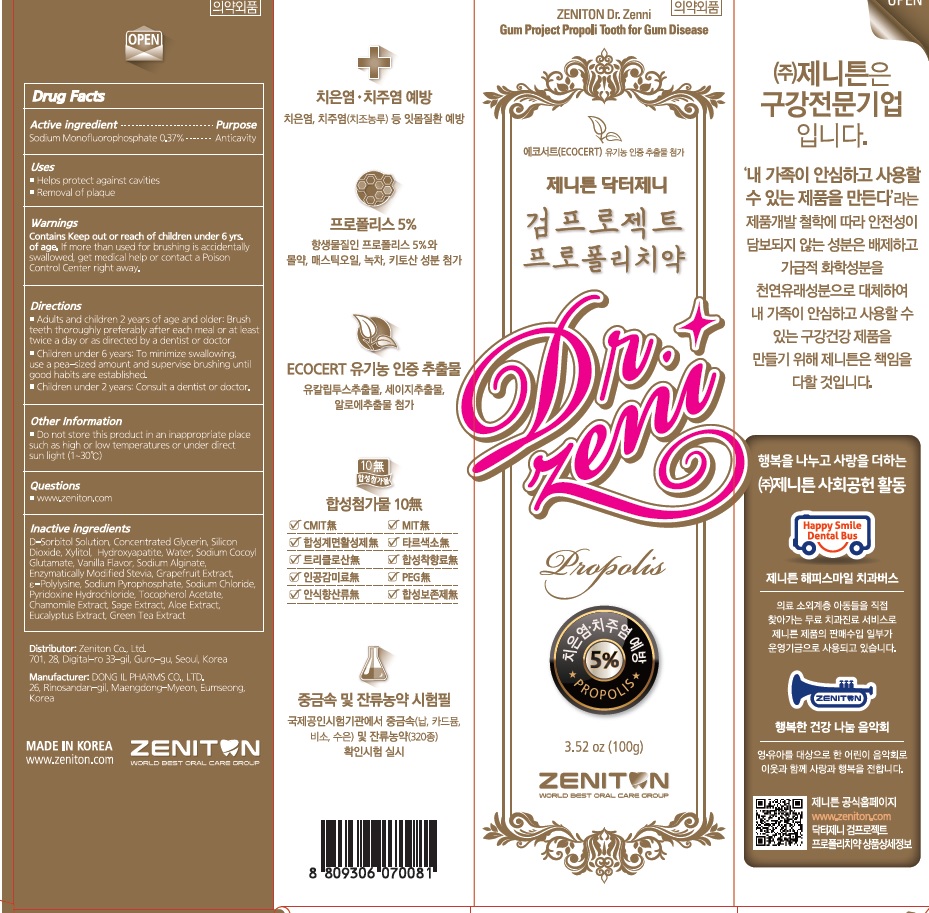 DRUG LABEL: Dr. Zenni Gum Project Propoli Tooth for Gum Disease
NDC: 73029-0006 | Form: PASTE, DENTIFRICE
Manufacturer: Zeniton Co.,Ltd.
Category: otc | Type: HUMAN OTC DRUG LABEL
Date: 20211228

ACTIVE INGREDIENTS: SODIUM MONOFLUOROPHOSPHATE 0.7581 g/100 g
INACTIVE INGREDIENTS: XYLITOL; WATER

ACTIVE INGREDIENT

Sodium Monofluorophosphate 0.75%

PURPOSE

Anticavity

Keep out of reach of children

Uses

■ Helps protect against cavities
■ Removal of plaque

WARNINGS

Keep out or reach of children under 6 yrs. of age. If more than used for brushing is accidentally swallowed, get medical help or contact a Poison Control Center right away.

INACTIVE INGREDIENTS

D-Sorbitol Solution, Silicon Dioxide, Water, Concentrated Glycerin, Propolis Extract, Sodium Chloride, Sodium Cocoyl Glutamate, Xanthangum, Peppermint Oil, Aminocaproic Acid, Aluminum Chlorohydroxy Allantoinate, Grapefruit Seed Extract, Xylitol, Tocopherol Acetate, Calendula Extract, Eucalyptus Extract, Green Tea Extract, Sage Extract, Aloe Extract, Mastic Oil, Myrrh, Chitosan

Directions

■ Adults and children 2 years of age and older: Brush teeth thoroughly preferably after each meal or at least twice a day or as directed by a dentist or doctor.
■ Children under 6 years: To minimize swallowing, use a pea-sized amount and supervise brushing until good habits are established.
■ Children under 2 years: Consult a dentist or doctor.

Other Information

■ Do not store this product in an inappropriate place such as high or low temperatures or under direct sun light (1~30℃)

QUESTIONS

■ www.zeniton.com